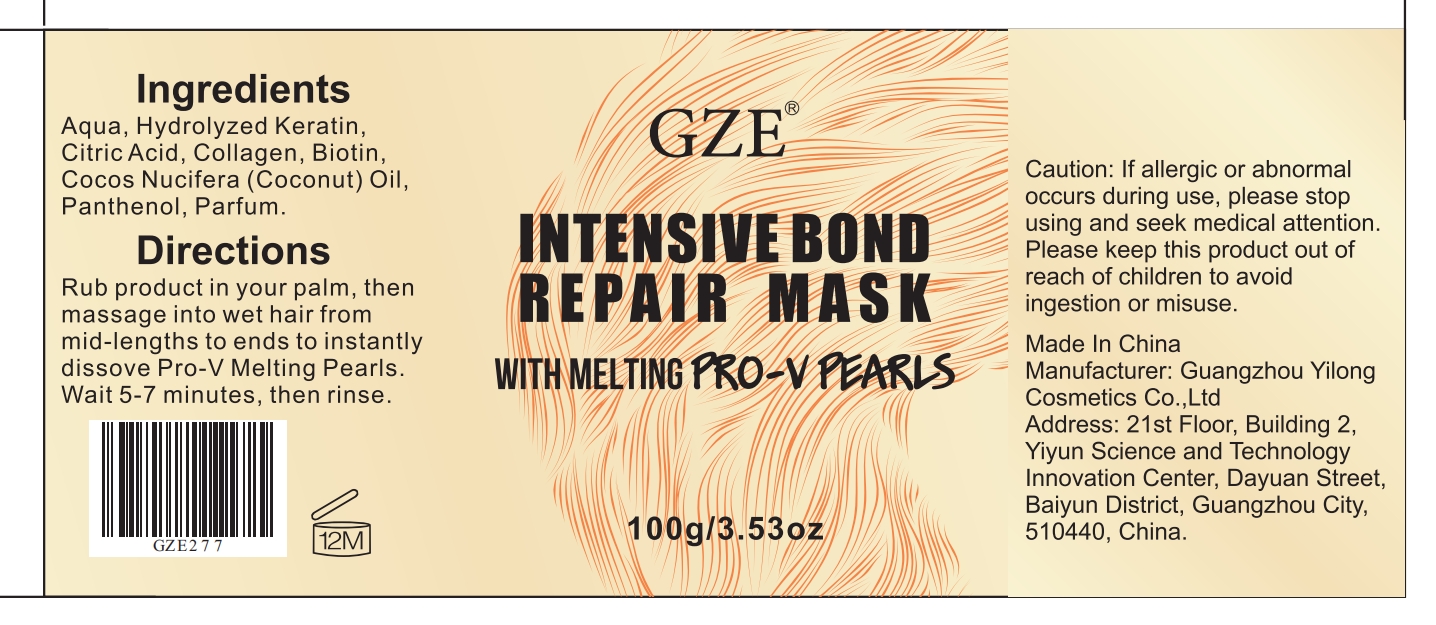 DRUG LABEL: GZE INTENSIVE BOND REPAIR MASK
NDC: 74458-278 | Form: CREAM
Manufacturer: Guangzhou Yilong Cosmetics Co., Ltd
Category: otc | Type: HUMAN OTC DRUG LABEL
Date: 20241011

ACTIVE INGREDIENTS: AMINO ACIDS, HAIR KERATIN 22.8 g/100 g; BIOTIN 2 g/100 g; PANTHENOL 2 g/100 g
INACTIVE INGREDIENTS: CITRIC ACID MONOHYDRATE; PARFUMIDINE; COCONUT OIL; WATER

GZE INTENSIVE BOND REPAIR MASK

ACTIVE INGREDIENT

Hydrolyzed Keratin, Biotin, Panthenol

INACTIVE INGREDIENT

Aqua, Citric Acid, Cocos Nucifera (Coconut) Oil,Parfum.

INDICATIONS AND USAGE

Rub product in your palm, then massage into wet hair from mid-lengths to ends to instantly dissove Pro-V Melting Pearls. Wait 5-7 minutes, then rinse.

WARNINGS

For external use only.

Stop use and ask a doctor if rash occurs.

Do not use on damaged or broken skin.

When using this product keep out of eyes. Rinse with water to remove.

Keep out of reach of children. If swallowed, get medical help or contact a Poison Control Center right away.

DOSAGE AND ADMINISTRATION

Rub product in your palm, then massage into wet hair from mid-lengths to ends to instantly dissove Pro-V Melting Pearls. Wait 5-7 minutes, then rinse.

PURPOSE

Moisturises dry hair.